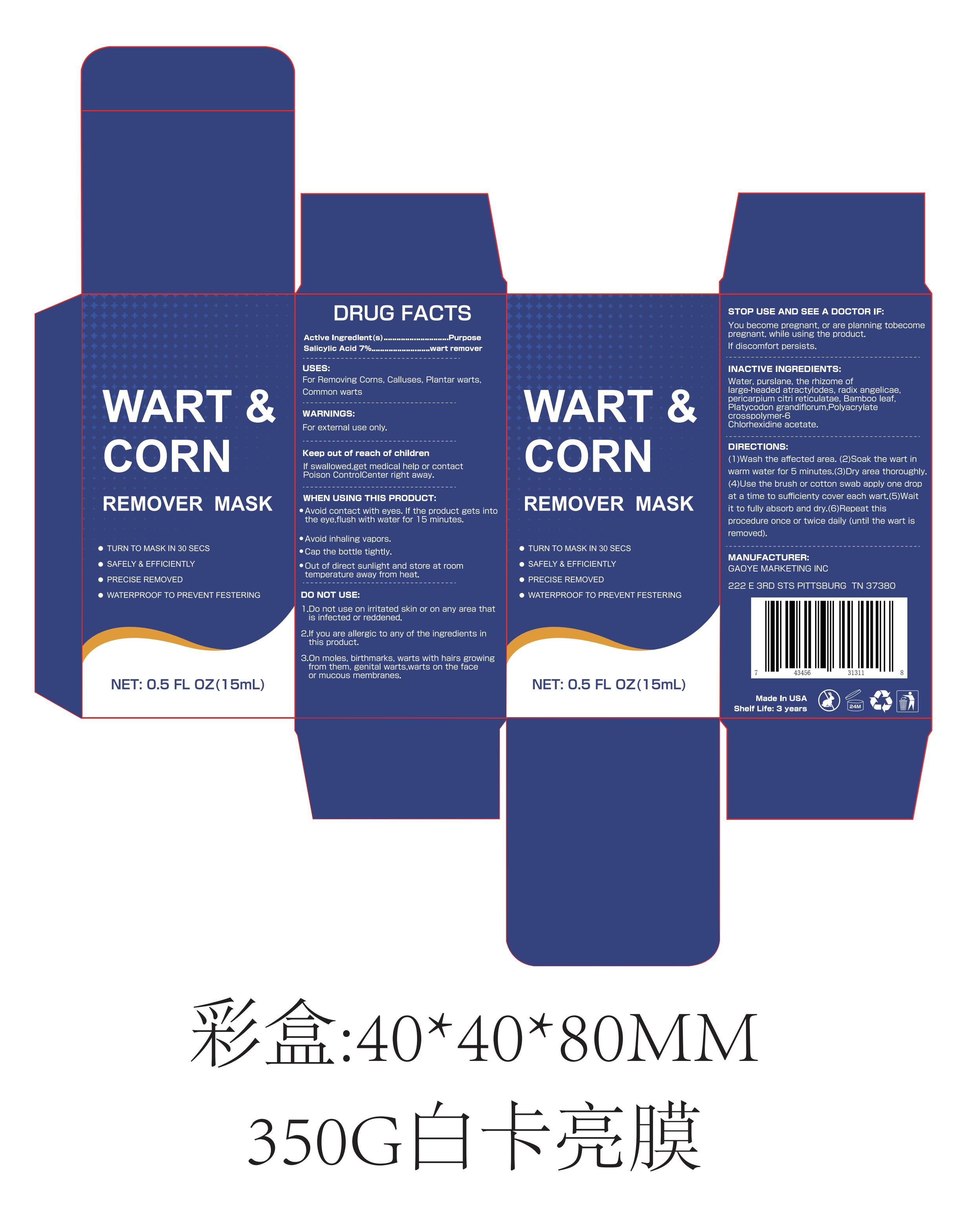 DRUG LABEL: WART CORN REMOVER MASK
NDC: 85308-001 | Form: LIQUID
Manufacturer: Gaoye Marketing Inc
Category: otc | Type: HUMAN OTC DRUG LABEL
Date: 20250307

ACTIVE INGREDIENTS: SALICYLIC ACID 7 g/100 mL
INACTIVE INGREDIENTS: ATRACTYLODES MACROCEPHALA ROOT; ANGELICA DAHURICA ROOT; BAMBUSA VULGARIS LEAF; PLATYCODON GRANDIFLORUM ROOT; POLYACRYLATE CROSSPOLYMER-6; PURSLANE; TANGERINE PEEL; WATER; CHLORHEXIDINE ACETATE

85308-001

Active Ingredient

Salicylic Acid 7%

Purpose

Wart remover

Use

For Removing Corns, Calluses, Plantar warts, Common warts

Warnings

For external use only.

Do not use on irritated skin or on any area that is infected or reddened.
If you are allergic to any of the ingredients in this product.
On moles, birthmarks, warts with hairs growing from them, genital warts, warts on the face or mucous membranes.

When Using

Avoid contact with eyes. If the product gets into the eye, flush with water for 15 minutes.
Avoid inhaling vapors.
Cap the bottle tightly.
Out of direct sunlight and store at room temperature away from heat.

Stop Use

You become pregnant, or are planning to become pregnant, while using the product.
If discomfort persists.

Ask Doctor

You become pregnant, or are planning to become pregnant, while using the product.
If discomfort persists.

Keep Oot Of Reach Of Children

If swallowed, get medical help or contact Poison Control Center right away.

Directions

(1) Wash the affected area.

(2) Soak the wart in warm water for 5 minutes.

(3) Dry area thoroughly.

(4) Use the brush or cotton swab apply one drop at a time to sufficiently cover wart.

(5) Wait for it to fully absorb and dry.

(6) Repeat this procedure once or twice daily (until the wart is removed).

Inactive ingredients

Water, purslane, the rhizome of angelicae, large-headed atractylodes, radix angelicae, pericarpium citri reticulatae, bamboo leaf,

Platycodon grandiflorum, Polyacrylate Chlorypolymer-6, Chlorhexidine acetate.